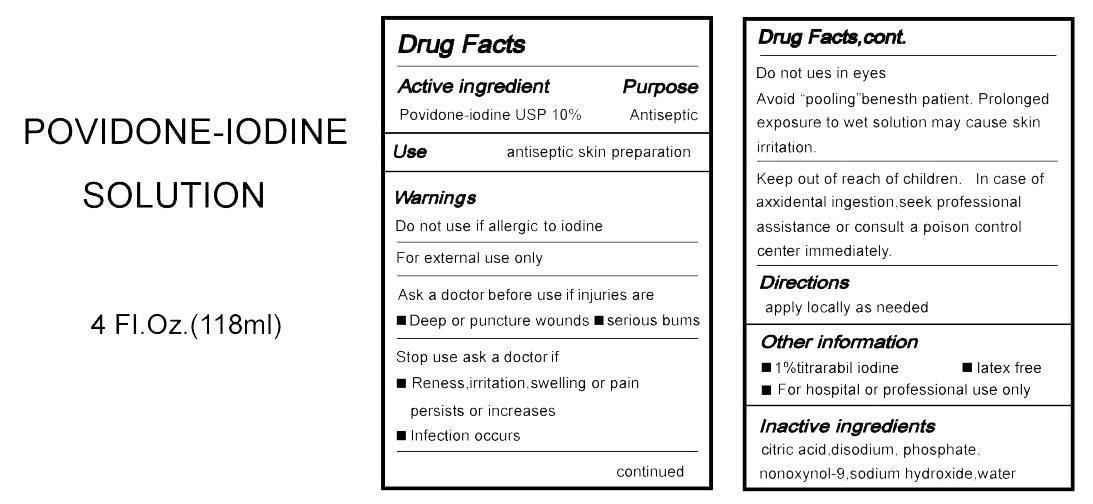 DRUG LABEL: Povidone-Iodine Solution
NDC: 58488-006 | Form: SOLUTION
Manufacturer: Tongzhou Ruihong Medical Products Factory
Category: otc | Type: HUMAN OTC DRUG LABEL
Date: 20140526

ACTIVE INGREDIENTS: POVIDONE-IODINE 0.01 mg/1 g
INACTIVE INGREDIENTS: WATER; CITRIC ACID MONOHYDRATE; SODIUM PHOSPHATE, DIBASIC; SODIUM HYDROXIDE; NONOXYNOL-9

Drug Fact

Active Ingredient

POVIDONE-IODINE USP 10%

Purpose

Antiseptic

Warnings

Do not use if allergic to iodine.

For External use only.

Ask a doctor before use if injuries are

--Deep or puncture wounds

--serious bums

stop use ask a doctor if

--reness ,irritation ,swelling or pain persists or increases

--infection occurs

Do not use in eyes

Avoid "pooling "benesth patient.Prolonged exposure to wet solution may cause skin irrtation.

Keep out of reach of children.in case of axxidental ingestion,seek professional assistance or consult a poison control center immediately.

Directions

Apple locally as needed.

Other information

--1% titrarabil iodine --latex free ---for hospital or professional use only

Use

Antiseptic skin preparation

Inactive Ingredients

citric acid,disodium,phosphate,nonoxynol-9,sodium hydrexide,Water